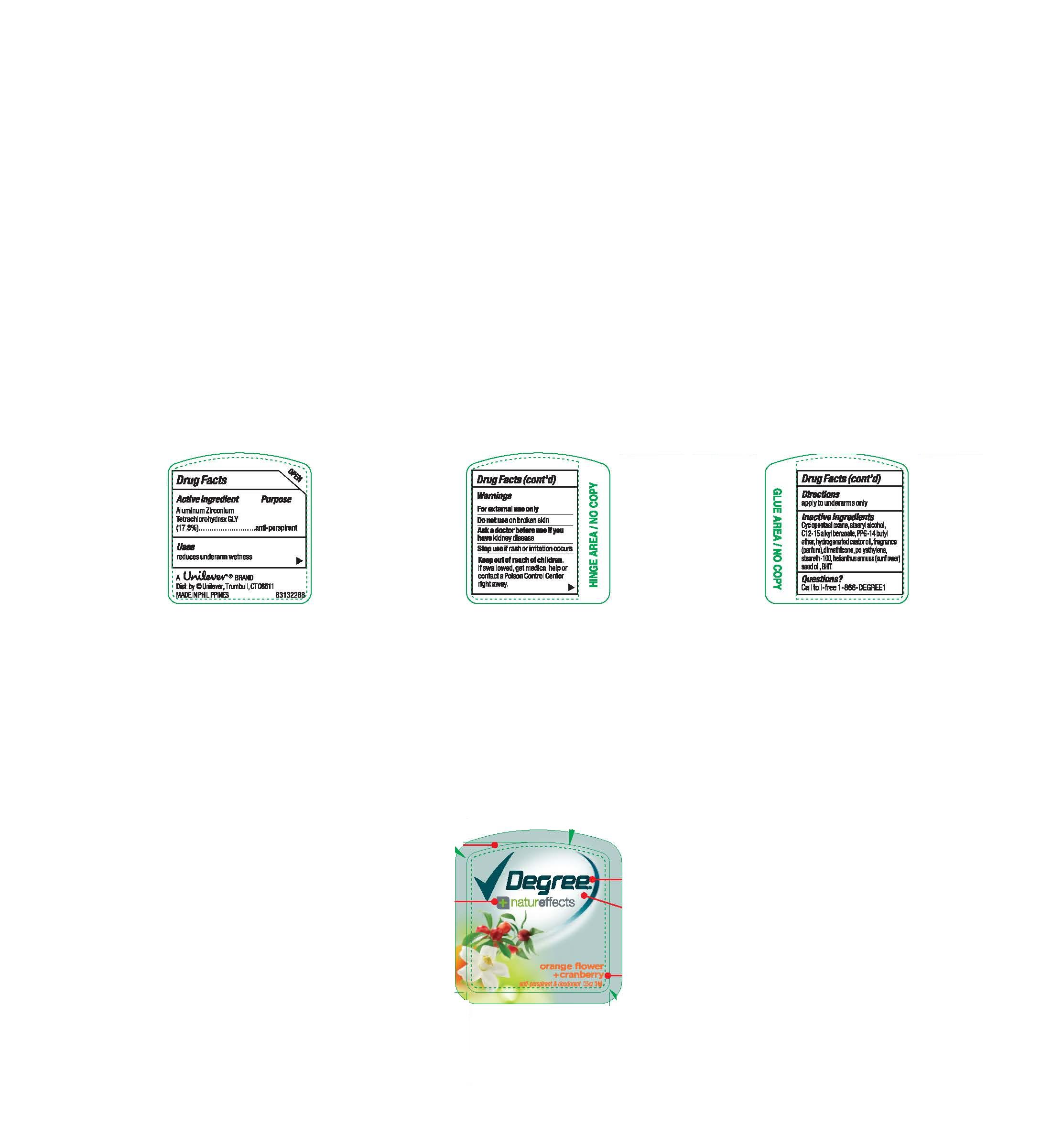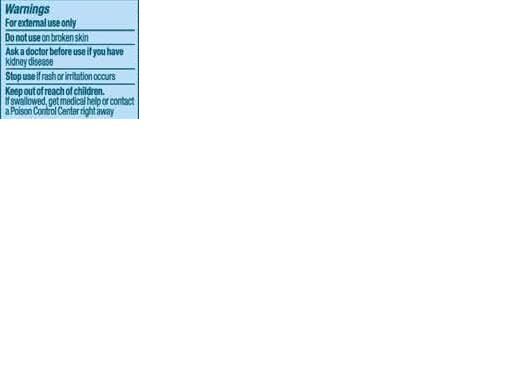 DRUG LABEL: Degree Women
NDC: 64942-0001 | Form: STICK
Manufacturer: Conopco Inc. d/b/a Unilever
Category: otc | Type: HUMAN OTC DRUG LABEL
Date: 20100115

ACTIVE INGREDIENTS: Aluminum Zirconium Tetrachlorohydrex GLY 17.8 g/100 g

Degree Women Nature Effects Orange Flower and Cranberry Antiperspirant and Deodorant back and front PACKAGE LABEL.PRINCIPAL DISPLAY PANEL and Drug Facts

Active ingredient Purpose
Aluminum Zirconium Tetrachlorohydrex GLY (17.8%)........................antiperspirant

Ask a doctor before use if you have kidney disease.

Purpose

anti-perspirant

Uses

Uses reduces underarm wetness

Do not use on broken skin

Questions

Questions? call 1-866-DEGREE1

Keep out of reach of children.

If swallowed, get medical help or contact a Poison Control Center right away

Stop use if rash or irritation occurs.

Inactive ingredients

Inactive Ingredients Cyclopentasiloxane, Stearyl Alcohol, C12-15 Alkyl Benzoate, PPG-14 Butyl Ether, Hydrogenated Castor Oil, Fragrance (Parfum), Dimethicone, Polyethylene, Steareth-100, Helianthus Annuus (Sunflower) Seed Oil, BHT.

PACKAGE LABEL

PDP 0.5 oz front and back